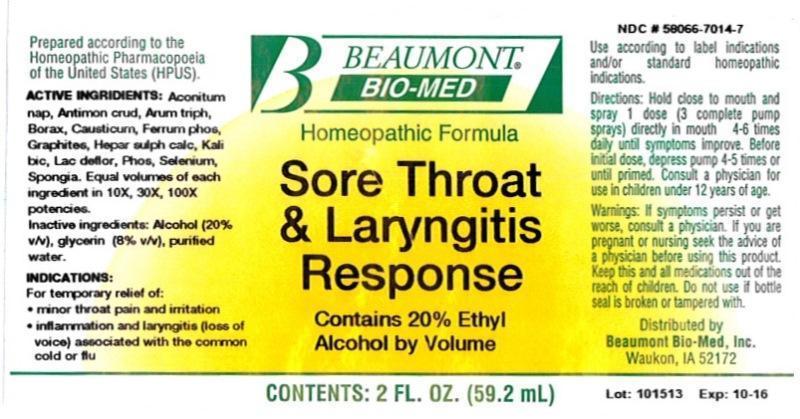 DRUG LABEL: Sore Throat and Laryngitis Response
NDC: 58066-7014 | Form: LIQUID
Manufacturer: Beaumont Bio Med
Category: homeopathic | Type: HUMAN OTC DRUG LABEL
Date: 20150108

ACTIVE INGREDIENTS: ACONITUM NAPELLUS 10 [hp_X]/59.2 mL; ANTIMONY TRISULFIDE 10 [hp_X]/59.2 mL; ARISAEMA TRIPHYLLUM ROOT 10 [hp_X]/59.2 mL; SODIUM BORATE 10 [hp_X]/59.2 mL; CAUSTICUM 10 [hp_X]/59.2 mL; FERROSOFERRIC PHOSPHATE 10 [hp_X]/59.2 mL; GRAPHITE 10 [hp_X]/59.2 mL; CALCIUM SULFIDE 10 [hp_X]/59.2 mL; POTASSIUM DICHROMATE 10 [hp_X]/59.2 mL; SKIM MILK 10 [hp_X]/59.2 mL; PHOSPHORUS 10 [hp_X]/59.2 mL; SELENIUM 10 [hp_X]/59.2 mL; SPONGIA OFFICINALIS SKELETON, ROASTED 10 [hp_X]/59.2 mL
INACTIVE INGREDIENTS: ALCOHOL; GLYCERIN; WATER

Sore Throat and Laryngitis

ACTIVE INGREDIENT

HPUS active ingredients: Aconitum napellus, Antimonium crudum, Arum triphyllum, Borax, Causticum, Ferrum phosphoricum, Graphites, Hepar sulphuris calcareum, Kali bichromicum, Lac defloratum, Phosphorus, Selenium metallicum, Spongia tosta. Equal volumes of each ingredient in 10X, 30X, 100X potencies.

INACTIVE INGREDIENT

Inactive Ingredients: Alcohol @ (20% v/v), Glycerin @ (8% v/v), in a pure water base.

INDICATIONS AND USAGE

Indications: For temporary relief of: •minor throat pain and irritation inflammation and laryngitis (loss of voice) associated with the common cold or flu.

Directions:

- Hold close to mouth and spray 1 dose (3 complete pump sprays) directly in mouth 4-6 times daily until symptoms improve.
- Before initial dose, depress pump 4-5 times or until primed.
- Consult a physician for use in children under 12 years of age.

Use according to label indications and/or standard homeopathic indications.

WARNINGS

Warnings: If symptoms persist or get worse, consult a physician. If you are pregnant or nursing seek the advice of a physician before using this product. Keep this and all medications out of the reach of children. Do not use if bottle seal is broken or tampered with.

- Keep out of reach of children.

PURPOSE

For temporary relief of:

- minor throat pain and irritation
- inflammation and laryngitis (loss of voice) associated with the common cold or flu